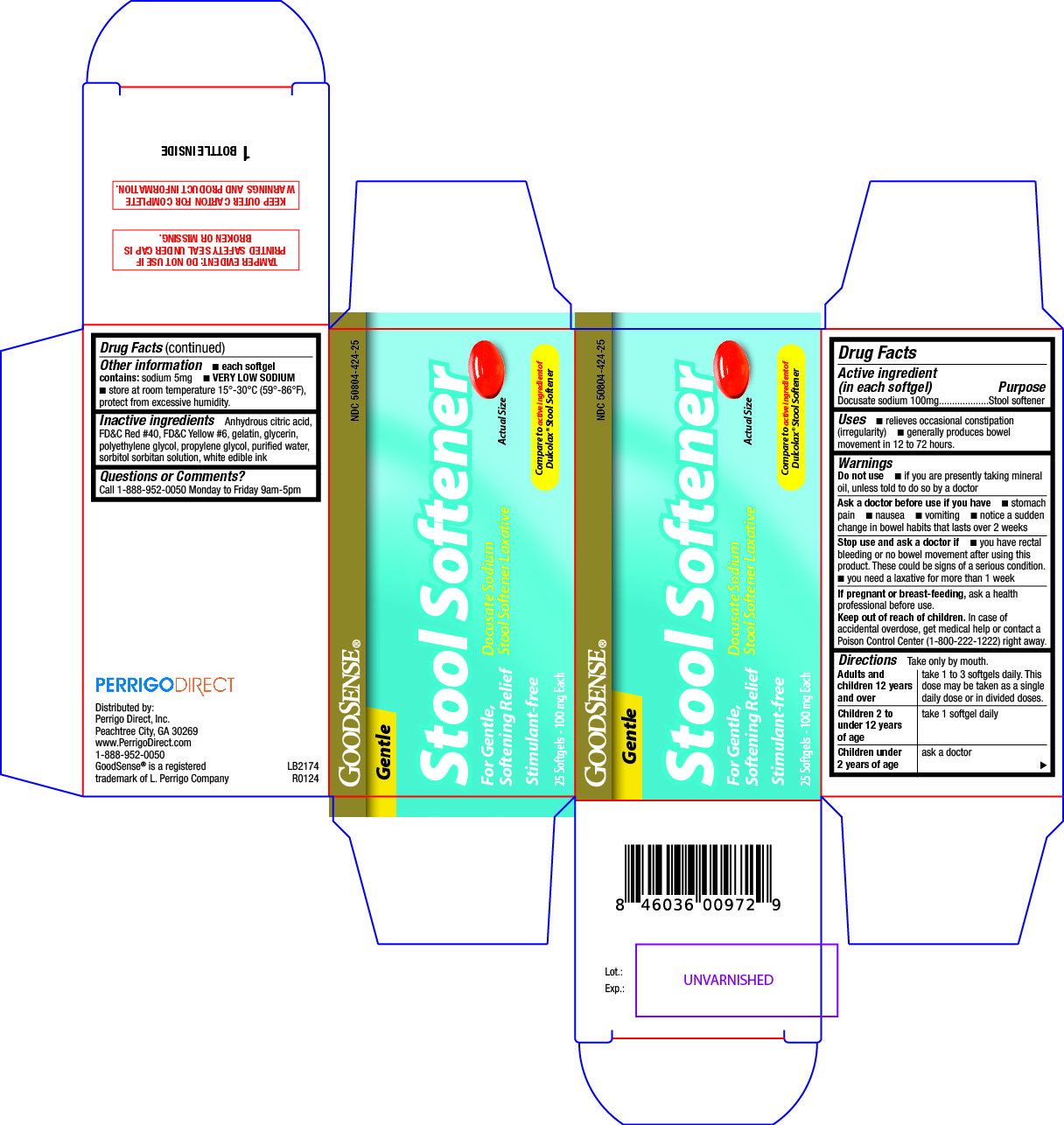 DRUG LABEL: Stool Softener
NDC: 50804-424 | Form: CAPSULE, LIQUID FILLED
Manufacturer: Good Sense
Category: otc | Type: HUMAN OTC DRUG LABEL
Date: 20240618

ACTIVE INGREDIENTS: DOCUSATE SODIUM 100 mg/1 1
INACTIVE INGREDIENTS: ANHYDROUS CITRIC ACID; FD&C RED NO. 40; FD&C YELLOW NO. 6; GELATIN; GLYCERIN; POLYETHYLENE GLYCOL, UNSPECIFIED; PROPYLENE GLYCOL; WATER; SORBITOL SOLUTION

424 - Stool Softener

Active ingredient(s)

Docusate sodium 100mg

Purpose

Stool softener

Use(s)

- relieves occasional constipation (irregularity)
- generally produces bowel movement in 12 to 72 hours

Warnings

Do not use

- if you are presently taking mineral oil, unless told to do so by a doctor

Ask a doctor before use if

- stomach pain
- nausea
- vomiting
- notice a sudden change in bowel habits that lasts over 2 weeks

Stop use and ask a doctor if

- you have rectal bleeding or no bowel movement after using this product. These could be signs of a serious condition.
- you need a laxative for more than 1 week

If pregnant or breastfeeding,

ask a health professional before use.

Keep out of reach of children

In case of accidental overdose, get medical help or contact a Poison Control Center (1-800-222-1222) right away.

Directions

Take only by mouth.

Adults and children 12 years and over: take 1 to 3 softgels daily. This dose may be taken as a single daily dose or in divided doses.

Children 2 to under 12 years of age: take 1 softgel daily

Children under 2 years of age: ask a doctor

Other information

- each softgel contains: sodium 5mg
- VERY LOW SODIUM
- do not use if imprinted safety seal under cap is broken or missing
- Store at room temperature 15°-30°C (59°-86°F), protect from excessive humidity.

Inactive ingredients

Anhydrous citric acid, FD&C Red #40, FD&C Yellow #6, gelatin, glycerin, polyethylene glycol,

propylene glycol, purified water, sorbitol sorbitan solution and white edible ink.

Questions/Comments

Call 1-888-952-0050 Monday to Friday 9am-5pm

Principal Display Panel

Stool Softener